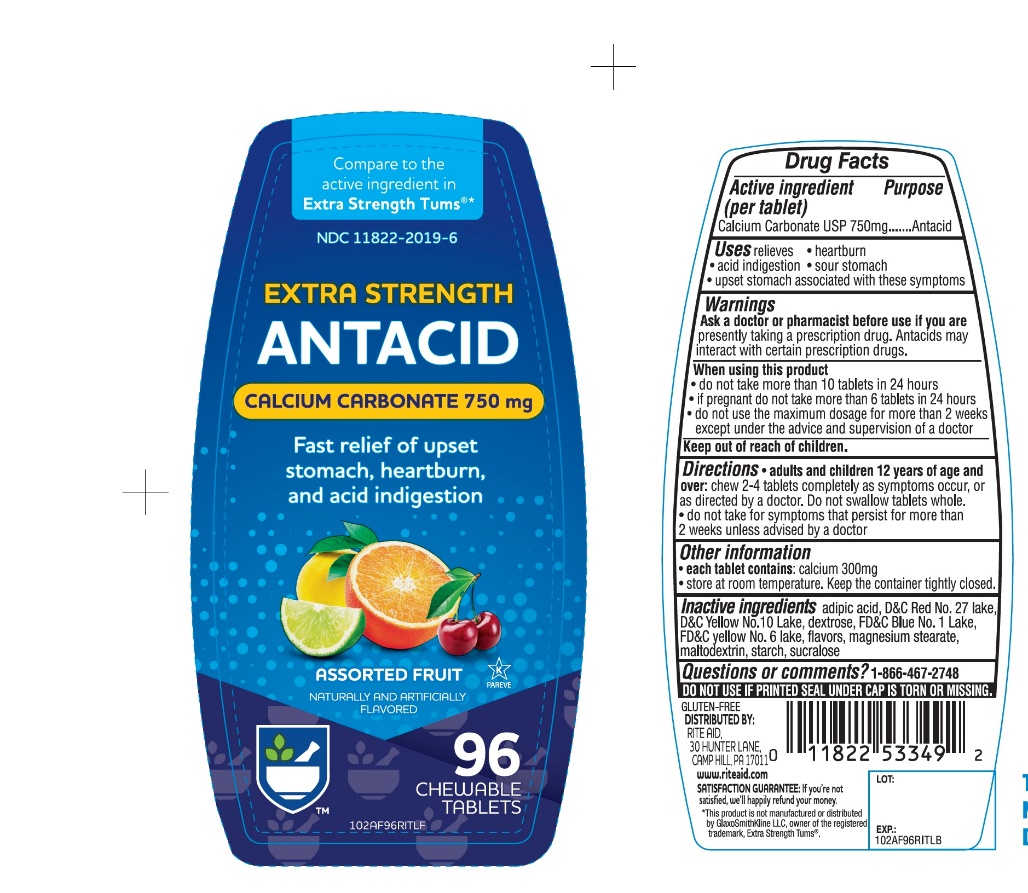 DRUG LABEL: Rite Aid Extra Strength
NDC: 11822-2019 | Form: TABLET, CHEWABLE
Manufacturer: RITE AID CORPORATION
Category: otc | Type: HUMAN OTC DRUG LABEL
Date: 20241030

ACTIVE INGREDIENTS: CALCIUM CARBONATE 750 mg/1 1
INACTIVE INGREDIENTS: ADIPIC ACID; D&C RED NO. 27; D&C YELLOW NO. 10; DEXTROSE, UNSPECIFIED FORM; FD&C BLUE NO. 1; FD&C YELLOW NO. 6; MAGNESIUM STEARATE; MALTODEXTRIN; STARCH, CORN; SUCRALOSE

RITE AID Extra Strength Assorted Fruit Antacid Tablets Drug Facts

Active ingredient (per tablet)

Calcium Carbonate USP 750mg

Purpose

Antacid

Uses

relieves

- heartburn
- sour stomach
- acid indigestion
- upset stomach associated with these symptoms

Warnings

Ask a doctor or pharmacist before use if you are

- presently taking a prescription drug. Antacids may interact with certain prescription drugs.

When using this product

- do not take more than 10 tablets in 24 hours
- if pregnant do not take more than 6 tablets in 24 hours
- do not use the maximum dosage for more than 2 weeks except under the advice and supervision of a doctor

Directions

- adults and children 12 years of age and over: chew 2 - 4 tablets as symptoms occur, or as directed by a doctor. Do not swallow tablets whole.
- do not take for symptoms that persist for more than 2 weeks unless advised by a doctor

Other information

- each tablet contains: elemental calcium 300 mg
- Store at room temperature. Keep the container tightly closed.

Inactive ingredients

adipic acid, D&C Red No. 27, D&C Yellow No. 10, dextrose, FD &C Blue No. 1, FD&C Yellow No. 6, flavors, magnesium stearate, maltodextrin, starch, sucrose.

Questions or comments?

1-866-467-2748

SAFETY SEALED. DO NOT USE IF PRINTED SEAL UNDER CAP IS TORN OR MISSING.

Principal Display Panel

NDC 11822-2019-6

RITE AID PHARMACY®

*Compare to the active ingredient Extra Strength Tums®

EXTRA STRENGTH

ANTACID

CALCIUM CARBONATE 750 MG

ASSORTED FRUIT

NATURALLY AND ARTIFICIALLY FLAVORED

Fast Relief of Upset Stomach, Heartburn and Acid Indigestion

K PAREVE

96 CHEWABLE TABLETS

GLUTEN FREE

DISTRIBUTED BY: RITE AID

30 HUNTER LANE, CAMP HILL, PA 17011

www.riteaid.com

SATISFACTION GUARANTEE :

if you’re not satisfied we ‘ll happily refund your money.

*This product is not manufactured or distributed by GlaxoSmithKline LLC, owner of the registered trademark, Extra Strength Tums®